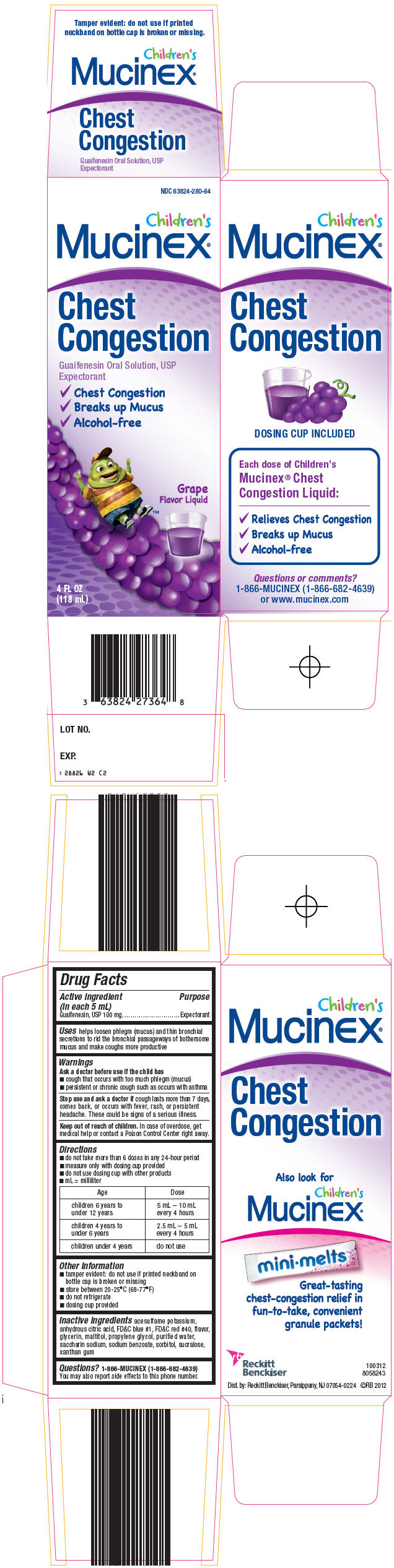 DRUG LABEL: Childrens Mucinex Chest Congestion
NDC: 63824-280 | Form: LIQUID
Manufacturer: Reckitt Benckiser LLC
Category: otc | Type: HUMAN OTC DRUG LABEL
Date: 20121109

ACTIVE INGREDIENTS: Guaifenesin 100 mg/5 mL
INACTIVE INGREDIENTS: acesulfame potassium; anhydrous citric acid; FD&C blue no. 1; FD&C red no. 40; glycerin; maltitol; propylene glycol; water; saccharin sodium; sodium benzoate; sorbitol; sucralose; xanthan gum

Childrens
Mucinex®
Chest
Congestion

Drug Facts

Active ingredient (in each 5 mL)

Guaifenesin, USP 100 mg

Purpose

Expectorant

Uses

helps loosen phlegm (mucus) and thin bronchial secretions to rid the bronchial passageways of bothersome mucus and make coughs more productive

Warnings

Ask a doctor before use if the child has

- cough that occurs with too much phlegm (mucus)
- persistent or chronic cough such as occurs with asthma

Stop use and ask a doctor if cough lasts more than 7 days, comes back, or occurs with fever, rash, or persistent headache. These could be signs of a serious illness.

Keep out of reach of children. In case of overdose, get medical help or contact a Poison Control Center right away.

Directions

- do not take more than 6 doses in any 24-hour period
- measure only with dosing cup provided
- do not use dosing cup with other products
- mL = milliliter

Age | Dose
children 6 years to under 12 years | 5 mL – 10 mL every 4 hours
children 4 years to under 6 years | 2.5 mL – 5 mL every 4 hours
children under 4 years | do not use

Other information

- tamper evident: do not use if printed neckband on bottle cap is broken or missing
- store between 20-25°C (68-77°F)
- do not refrigerate
- dosing cup provided

Inactive ingredients

acesulfame potassium, anhydrous citric acid, FD&C blue #1, FD&C red #40, flavor, glycerin, maltitol, propylene glycol, purified water, saccharin sodium, sodium benzoate, sorbitol, sucralose, xanthan gum

Questions?

1-866-MUCINEX (1-866-682-4639)

You may also report side effects to this phone number.

PRINCIPAL DISPLAY PANEL - 118 mL Bottle Carton

NDC 63824-280-64

Children's
Mucinex®

Chest
Congestion

Guaifenesin Oral Solution, USP
Expectorant

✓ Chest Congestion
✓ Breaks up Mucus
✓ Alcohol-free

Grape
Flavor Liquid

4 FL OZ
(118 mL)